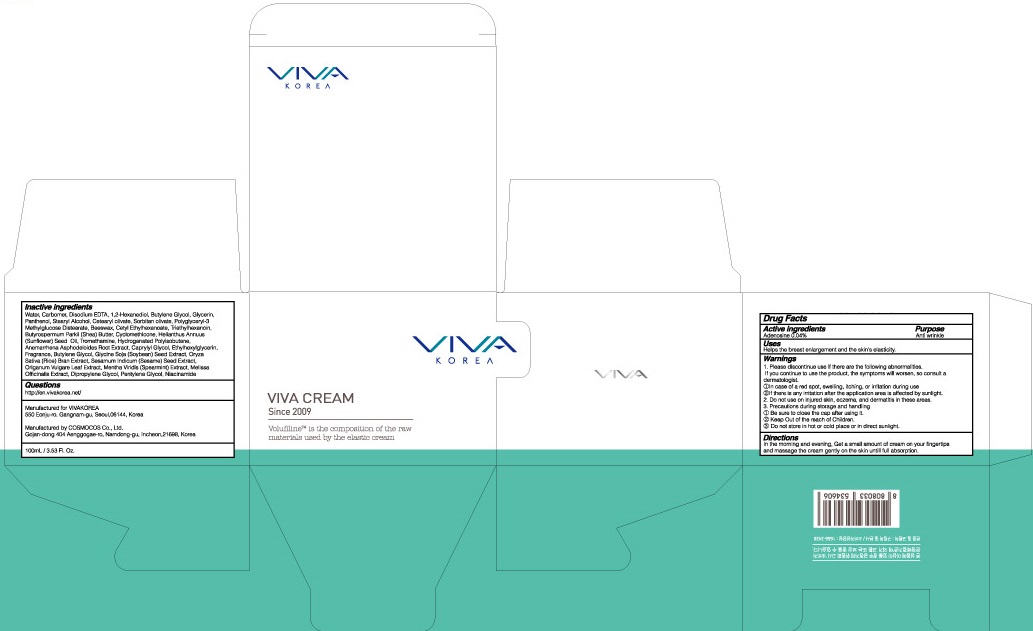 DRUG LABEL: VIVA
NDC: 72397-010 | Form: CREAM
Manufacturer: VIVAKOREA
Category: otc | Type: HUMAN OTC DRUG LABEL
Date: 20180706

ACTIVE INGREDIENTS: Adenosine 0.04 g/100 mL
INACTIVE INGREDIENTS: Water; Glycerin

ACTIVE INGREDIENT

Active ingredients: Adenosine 0.04%

INACTIVE INGREDIENT

Inactive ingredients:

Water, Carbomer, Disodium EDTA, 1,2-Hexanediol, Butylene Glycol, Glycerin, Panthenol, Stearyl Alcohol, Cetearyl olivate, Sorbitan olivate, Polyglyceryl-3 Methylglucose Distearate, Beeswax, Cetyl Ethylhexanoate, Triethylhexanoin, Butyrospermum Parkii (Shea) Butter, Cyclomethicone, Helianthus Annuus (Sunflower) Seed Oil, Tromethamine, Hydrogenated Polyisobutene, Anemarrhena Asphodeloides Root Extract, Caprylyl Glycol, Ethylhexylglycerin, Fragrance, Butylene Glycol, Glycine Soja (Soybean) Seed Extract, Oryza Sativa (Rice) Bran Extract, Sesamum Indicum (Sesame) Seed Extract, Origanum Vulgare Leaf Extract, Mentha Viridis (Spearmint) Extract, Melissa Officinalis Extract, Dipropylene Glycol, Pentylene Glycol, Niacinamide

PURPOSE

Purpose: Anti wrinkle

WARNINGS

1. Please discontinue use if there are the following abnormalities. If you continue to use the product, the symptoms will worsen, so consult a dermatologist. ①In case of a red spot, swelling, itching, or irritation during use ②If there is any irritation after the application area is affected by sunlight.

2. Do not use on injured skin, eczema, and dermatitis in these areas.

3. Precautions during storage and handling ① Be sure to close the cap after using it. ② Keep Out of the reach of Children. ③Do not store in hot or cold place or in direct sunlight.

KEEP OUT OF REACH OF CHILDREN

Uses

Helps the breast enlargement and the skin's elasticity.

Directions

In the morning and evening, Get a small amount of cream on your fingertips and massage the cream gently on the skin until full absorption.